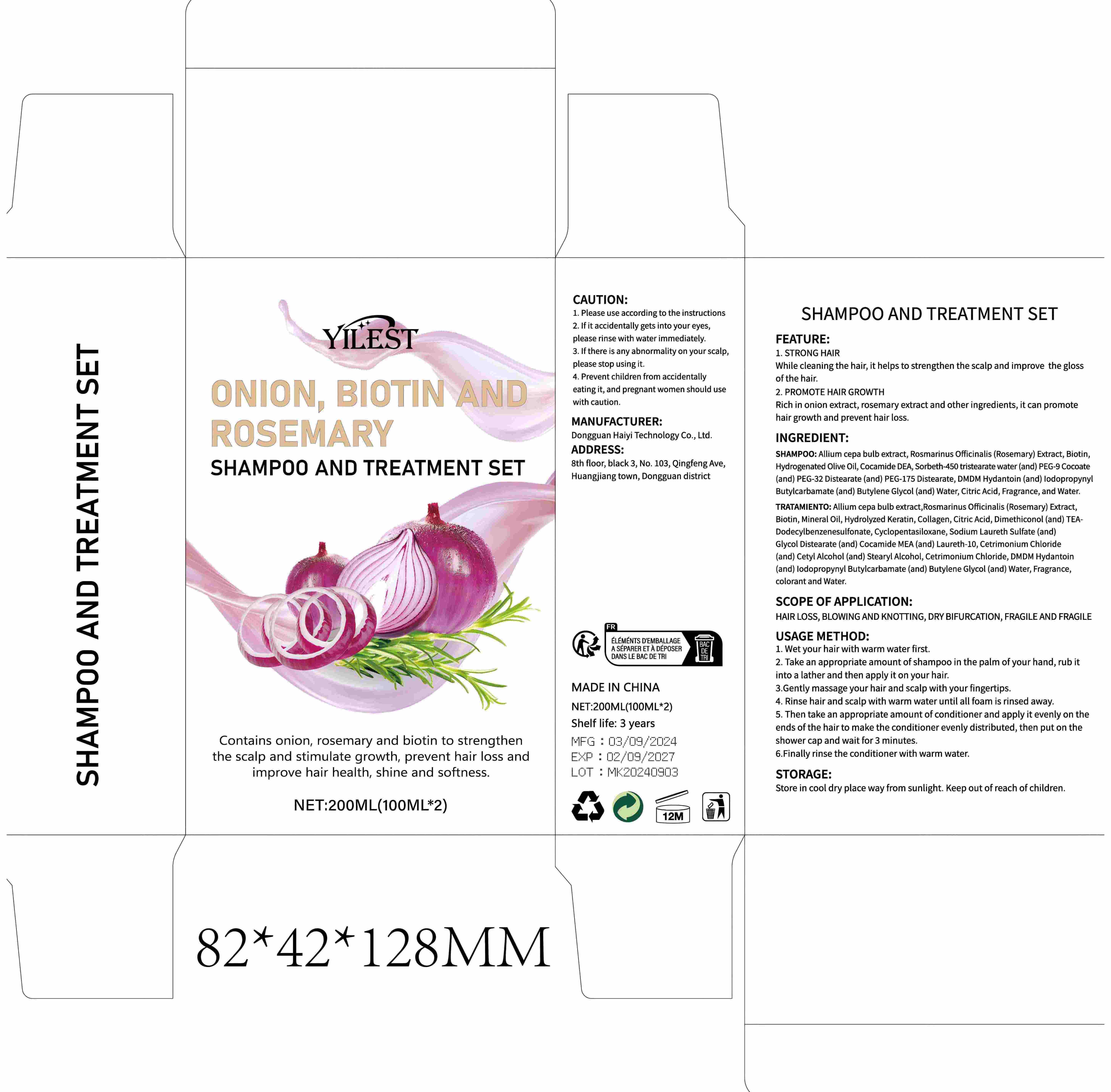 DRUG LABEL: ONION, BIOTIN AND ROSEMARY
NDC: 84732-004 | Form: CREAM
Manufacturer: Dongguan Haiyi Technology Co.,Ltd.
Category: otc | Type: HUMAN OTC DRUG LABEL
Date: 20240923

ACTIVE INGREDIENTS: ALLIUM CEPA WHOLE 1 mg/100 mL
INACTIVE INGREDIENTS: CITRIC ACID ACETATE; MINERAL OIL; COLLAGEN, SOLUBLE, FISH SKIN; DMDM HYDANTOIN; ROSMARINUS OFFICINALIS FLOWER; HYDROGENATED OLIVE OIL; DIMETHICONOL/TRIMETHYLSILOXYSILICATE CROSSPOLYMER (35/65 W/W; 10000000 PA.S); SORBETH-40 TETRAOLEATE; FRAGRANCE 13576; HAIR KERATIN AMINO ACIDS; COCAMIDE; BIOTIN; WATER; PENTAMETHYL CYCLOPENTASILOXANE

Active ingredient

Allium cepa bulb extract

Inactive ingredient

HAMP00: Allium cepa bulb extract, Rosmarinus Officinalis (Rosemary) Extract, Biotin,Hydrogenated Olive Oil, Cocamide DEA, Sorbeth-450 tristearate water (and) PEG-9 Cocoate(and) PEG-32 Distearate (and) PEG-175 Distearate, DMDM Hydantoin (and) lodopropyny!Butylcarbamate (and) Butylene Glycol (and) Water, Citric Acid, Fragrance, and Water.

TRATAMIENTO: Allium cepa bulb extract,Rosmarinus Officinalis (Rosemary) Extract,Biotin, Mineral Oil, Hydrolyzed Keratin, Collagen, Citric Acid, Dimethiconol (and) TEA-Dodecylbenzenesulfonate,Cyclopentasiloxane, Sodium Laureth Sulfate (and)Glycol Distearate (and) Cocamide MEA (and) Laureth-10,Cetrimonium Chloride(and) Cetyl Alcohol (and) Stearyl Alcohol, Cetrimonium Chloride, DMDM Hydantoin(and) lodopropynyl Butylcarbamate (and) Butylene Glycol (and) Water, Fragrance,colorant and Wate

Purpose section

1. STRONG HAIR

While cleaning the hair, it helps to strengthen the scalp and improve the glossof the hair.
2. PROMOTE HAIR GROWTH

Rich in onion extract, rosemary extract and other ingredients, it can promotehair growth and prevent hair loss.

Warning

1. Please use according to the instructions

2. lf it accidentally gets into your eyes,please rinse with water immediately.

3. lf there is any abnormality on your scalp,please stop using it.

4. Prevent children from accidentallyeatingit, and pregnant women should usewith caution.

stop use

lf there is any abnormality on your scalp,please stop using it.

not use

Prevent children from accidentallyeating it, and pregnant women should usewith caution.

OUT OF CHILDREN

KEEP THE PRODUCT OUT OF REACH OF CHILDREN to

HOW TO USE

1. Wet your hair with warm water first.

2. Take an appropriate amount of shampoo in the palm of your hand, rub itinto a lather and then apply it on your hair.

3.Gently massage your hair and scalp with your fingertips.

4. Rinse hair and scalp with warm water until all foam is rinsed away.

5. Then take an appropriate amount of conditioner and apply it evenly on theends of the hair to make the conditioner evenly distributed, then put on theshower cap and wait for 3 minutes.

6.Finally rinse the conditioner with warm water.

Dosage

take an appropriateamount,Use 2-3 times a week